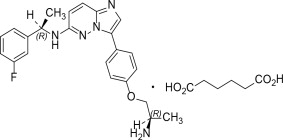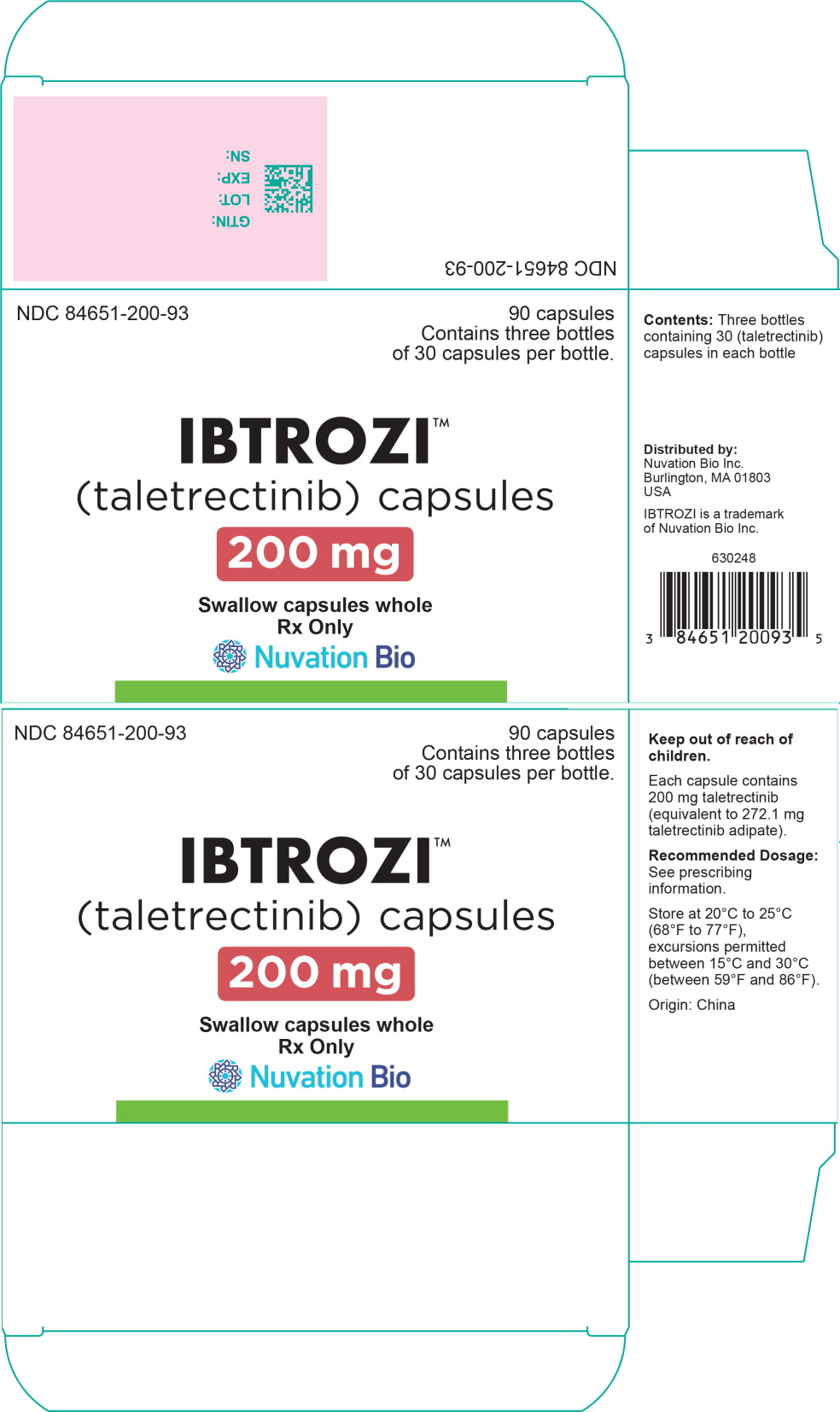 DRUG LABEL: IBTROZI
NDC: 84651-200 | Form: CAPSULE
Manufacturer: Nuvation Bio Inc.
Category: prescription | Type: HUMAN PRESCRIPTION DRUG LABEL
Date: 20250611

ACTIVE INGREDIENTS: taletrectinib adipate 272 mg/1 1
INACTIVE INGREDIENTS: mannitol; starch, corn; low-substituted hydroxypropyl cellulose, unspecified; silicon dioxide; sodium stearyl fumarate; hypromellose, unspecified; titanium dioxide; shellac; alcohol; isopropyl alcohol; butyl alcohol; propylene glycol; ammonia; FD&C Blue No. 1 Aluminum Lake

HIGHLIGHTS OF PRESCRIBING INFORMATION

These highlights do not include all the information needed to use IBTROZI safely and effectively. See full prescribing information for IBTROZI.
IBTROZITM (taletrectinib) capsules, for oral use
Initial U.S. Approval: 2025

1 INDICATIONS AND USAGE

IBTROZI is a kinase inhibitor indicated for the treatment of adult patients with locally advanced or metastatic ROS1-positive non-small cell lung cancer (NSCLC). (1)

2 DOSAGE AND ADMINISTRATION

- Select patients for the treatment of locally advanced or metastatic NSCLC based on the presence of ROS1 rearrangement(s). (2.1)
- Recommended Dosage: 600 mg orally once daily on an empty stomach (no food intake at least 2 hours before and 2 hours after taking IBTROZI). (2.3)
- Continue treatment until disease progression or unacceptable toxicity. (2.3)

3 DOSAGE FORMS AND STRENGTHS

Capsules: 200 mg of taletrectinib (3)

4 CONTRAINDICATIONS

- None (4)

5 WARNINGS AND PRECAUTIONS

- Hepatotoxicity: Monitor liver function tests prior to initiating, every 2 weeks during the first 2 months of treatment, then monthly thereafter as clinically indicated, with more frequent testing in patients who develop transaminase elevations. Based on severity and resolution, withhold and then resume at reduced dose, or permanently discontinue. (2.4, 5.1)
- Interstitial Lung Disease (ILD)/Pneumonitis: Monitor patients for new or worsening pulmonary symptoms indicative of ILD/pneumonitis. Immediately withhold in patients with suspected ILD/pneumonitis. Based on severity and resolution, resume at the same or reduced dose, or permanently discontinue. (2.4, 5.2)
- QTc Interval Prolongation: Monitor ECG and electrolytes prior to initiating and periodically during treatment. Based on severity and resolution, withhold and then resume at same or reduced dose, or permanently discontinue. (2.4, 5.3)
- Hyperuricemia: Monitor serum uric acid levels prior to initiating and periodically during treatment. Initiate treatment with urate-lowering medications as clinically indicated. Withhold and resume at same or reduced dose or permanently discontinue based on severity. (2.4, 5.4)
- Myalgia with Creatine Phosphokinase (CPK) Elevation: Monitor serum CPK levels during treatment in patients reporting unexplained muscle pain, tenderness, or weakness. Based on severity, withhold and resume at same or reduced dose upon improvement. (2.4, 5.5)
- Skeletal Fractures: Promptly evaluate patients with signs or symptoms (e.g., pain, changes in mobility, deformity) of fractures. (5.6)
- Embryo-Fetal Toxicity: Can cause fetal harm. Advise patients of the potential risk to a fetus and to use effective contraception. (5.7)

6 ADVERSE REACTIONS

The most frequently reported adverse reactions (≥20%) were: diarrhea, nausea, vomiting, dizziness, rash, constipation, and fatigue. (6.1)

The most frequently reported Grade 3 or 4 laboratory abnormalities (≥5%) were: increased ALT, increased AST, decreased neutrophils, and increased creatine phosphokinase. (6.1)

To report SUSPECTED ADVERSE REACTIONS, contact Nuvation Bio Inc. at 1-844-688-4550 or FDA at 1-800-FDA-1088 or www.fda.gov/medwatch.

7 DRUG INTERACTIONS

- Strong and Moderate CYP3A inhibitors: Avoid concomitant use. (7.1)
- Strong and Moderate CYP3A inducers: Avoid concomitant use. (7.1)
- Gastric Acid Reducing Agents: Avoid concomitant use with proton pump inhibitors (PPIs) and H2 receptor antagonists. If an acid-reducing agent cannot be avoided, administer IBTROZI 2 hours before or 2 hours after taking a locally acting antacid. (7.1)
- Drugs That Prolong the QTc Interval: Avoid concomitant use. (7.2)

8 USE IN SPECIFIC POPULATIONS

- Lactation: Advise not to breastfeed. (8.2)

FULL PRESCRIBING INFORMATION

1 INDICATIONS AND USAGE

IBTROZI™ (taletrectinib) is indicated for the treatment of adult patients with locally advanced or metastatic ROS1-positive non-small cell lung cancer (NSCLC) [see Dosage and Administration (2.1)].

2 DOSAGE AND ADMINISTRATION

2.1 Patient Selection

Select patients for the treatment of locally advanced or metastatic NSCLC with IBTROZI based on the presence of ROS1 rearrangement(s) in tumor specimens [see Clinical Studies (14.1)].

An FDA-approved test to detect ROS1 rearrangement(s) for selecting patients for treatment with IBTROZI is not currently available.

2.2 Recommended Testing and Evaluation Before Initiating IBTROZI

- Before initiating IBTROZI, evaluate liver function tests (including ALT, AST, and bilirubin), electrolytes, ECG, and uric acid [see Warnings and Precautions (5.1, 5.3, 5.4)].

2.3 Recommended Dosage and Administration

- The recommended dosage of IBTROZI is 600 mg orally once daily on an empty stomach (no food intake at least 2 hours before and 2 hours after taking IBTROZI) [see Clinical Pharmacology (12.2, 12.3)] until disease progression or unacceptable toxicity.
- Take IBTROZI at approximately the same time each day. Swallow IBTROZI capsules whole. Do not open, chew, crush, or dissolve the capsule prior to swallowing.
- Avoid food or drink containing grapefruit during treatment with IBTROZI.
- Minimize sun exposure and use sun protection, including broad-spectrum sunscreen, during treatment with IBTROZI and for at least 5 days after discontinuation [see Adverse Reactions (6.1)].

Missed Dose

- If a dose is missed, take the next dose at its scheduled time on the following day.

Vomiting

- If vomiting occurs at any time after taking a dose, take the next dose at its scheduled time on the following day.

2.4 Dosage Modifications for Adverse Reactions

The recommended dosage reductions for the management of adverse reactions are provided in Table 1.

Table 1: Recommended Dose Reductions for IBTROZI Adverse Reactions
Dosage Reduction | Recommended Dosage
First Dose Reduction | 400 mg once daily
Second Dose Reduction | 200 mg once daily
Permanently discontinue IBTROZI capsules in patients unable to tolerate 200 mg once daily.

The recommended dosage modifications of IBTROZI for the management of adverse reactions are provided in Table 2.

Table 2: Recommended Dosage Modifications for IBTROZI Adverse Reactions
Adverse Reaction | Severity* | Dosage Modification
Hepatotoxicity (Elevation of ALT or AST) [see Warnings and Precautions (5.1)] | Grade 3 (>5 - 20 × ULN) | Withhold IBTROZI until recovery to Grade ≤1 or baseline.; - If resolved within 6 weeks, resume IBTROZI at a reduced dose level. - If unresolved after 6 weeks, permanently discontinue IBTROZI.; Recurrence:; - If resolved within 6 weeks, resume IBTROZI at a reduced dose level. - If unresolved after 6 weeks, permanently discontinue IBTROZI.
Hepatotoxicity (Elevation of ALT or AST) [see Warnings and Precautions (5.1)] | Grade 4 (>20 × ULN) | Withhold IBTROZI until recovery to Grade ≤1 or baseline.; - If resolved within 6 weeks, resume IBTROZI at a reduced dose level. - If unresolved after 6 weeks, permanently discontinue IBTROZI.; Recurrence:; - Permanently discontinue IBTROZI.
Hepatotoxicity (Elevation of ALT or AST) [see Warnings and Precautions (5.1)] | ALT or AST ≥3 × ULN with concurrent total bilirubin ≥2 × ULN (in the absence of cholestasis or hemolysis) | - Permanently discontinue IBTROZI.
ILD/pneumonitis [see Warnings and Precautions (5.2)] | Grade 1 | Withhold IBTROZI if ILD/pneumonitis occurs or is suspected until recovery to Grade 0 or baseline.; - If resolved within 6 weeks, resume IBTROZI at the same dose level. - If unresolved after 6 weeks, permanently discontinue IBTROZI.; Recurrence:; - Permanently discontinue IBTROZI.
ILD/pneumonitis [see Warnings and Precautions (5.2)] | Grade 2 | Withhold IBTROZI if ILD/pneumonitis occurs or is suspected until recovery to Grade 0 or baseline.; - If resolved within 6 weeks, resume IBTROZI at a reduced dose level. - If unresolved after 6 weeks, permanently discontinue IBTROZI.; Recurrence:; - Permanently discontinue IBTROZI.
ILD/pneumonitis [see Warnings and Precautions (5.2)] | Grade 3 or 4 | - Permanently discontinue IBTROZI.
QTc Interval Prolongation [see Warnings and Precautions (5.3)] | Grade 2 (QTc interval 481-500 msec) | Withhold IBTROZI until recovery to Grade ≤1 or baseline.; - Correct electrolytes and/or change concomitant medications. - Resume IBTROZI at same dose.
QTc Interval Prolongation [see Warnings and Precautions (5.3)] | Grade 3 (QTc interval ≥501 msec or QTc interval increase of >60 msec from baseline) | Withhold IBTROZI until recovery to Grade ≤1 or baseline.; - Correct electrolytes and/or change concomitant medications. - Resume IBTROZI at a reduced dose.
QTc Interval Prolongation [see Warnings and Precautions (5.3)] | Grade 4 (Torsade de pointes; polymorphic ventricular tachycardia; signs/symptoms of serious arrhythmia) | Permanently discontinue IBTROZI.
Hyperuricemia [see Warnings and Precautions (5.4)] | Grade 3 or 4 | Withhold IBTROZI until improvement of signs or symptoms.; - Resume IBTROZI at same or reduced dose level or permanently discontinue.
Creatine Phosphokinase Elevation [see Warnings and Precautions (5.5)] | CPK elevation >5 times ULN | - Withhold until recovery to baseline or ≤2.5 times ULN, then resume at same dose.
Creatine Phosphokinase Elevation [see Warnings and Precautions (5.5)] | CPK elevation >10 times ULN or second occurrence of CPK elevation of >5 times ULN | - Withhold until recovery to baseline or ≤2.5 times ULN, then resume at a reduced dose.
Other Adverse Reactions [see Adverse Reactions (6.1)] | Grade 3 | Withhold IBTROZI until recovery to Grade ≤1 or baseline.; - If resolved within 6 weeks, resume IBTROZI at a reduced dose level. - If unresolved after 6 weeks, permanently discontinue IBTROZI.; Recurrence:; - Resume treatment at a reduced dose or permanently discontinue IBTROZI.
Other Adverse Reactions [see Adverse Reactions (6.1)] | Grade 4 | Withhold IBTROZI until recovery to Grade ≤1 or baseline. Resume IBTROZI at reduced dose or permanently discontinue as clinically indicated. Recurrence:; - Permanently discontinue IBTROZI.
Abbreviations: ALT = alanine aminotransferase; AST = aspartate aminotransferase; ULN = Upper limit of normal
*Graded per National Cancer Institute Common Terminology Criteria for Adverse Events (NCI CTCAE), version 5.0.

3 DOSAGE FORMS AND STRENGTHS

Capsules: 200 mg, immediate release, white, opaque, size 0, hard capsules filled with white to light yellow powder, imprinted with “TAL” and “200” in blue ink on the body of the capsule. Each capsule contains 272 mg of taletrectinib adipate equivalent to 200 mg of taletrectinib.

4 CONTRAINDICATIONS

None.

5 WARNINGS AND PRECAUTIONS

5.1 Hepatotoxicity

IBTROZI can cause hepatotoxicity, including drug-induced liver injury and fatal adverse reactions.

In the pooled safety population [see Adverse Reactions (6.1)], based on laboratory values, 88% of patients treated with IBTROZI experienced increased aspartate aminotransferase (AST), including 10% Grade 3 or 4. Increased alanine aminotransferase (ALT) occurred in 85% of patients treated with IBTROZI, including 13% Grade 3 or 4. The median time to first onset of AST or ALT elevation was 15 days (range: 3 days to 20.8 months).

Increased AST or ALT each led to dose interruption in 7% of patients. Increased AST and ALT leading to dose reduction occurred in 5% and 9% of patients, respectively. Increased AST and ALT each led to permanent discontinuation of IBTROZI in 0.3% of patients. Other liver-related adverse reactions leading to permanent discontinuation of IBTROZI were hepatotoxicity (0.6% of patients) and increased bilirubin (0.3% of patients).

Concurrent elevations in AST or ALT ≥3 times the upper limit of normal (ULN) and total bilirubin ≥2 times the ULN, with normal alkaline phosphatase, occurred in 2 (0.6%) patients treated with IBTROZI. Fatal liver events occurred in 2 (0.6%) patients.

Monitor liver function tests (AST, ALT, and bilirubin) prior to administration of IBTROZI, every 2 weeks during the first 2 months of treatment, and then monthly thereafter as clinically indicated with more frequent testing in patients who develop transaminase elevations. Withhold, then resume at reduced dose upon improvement, or permanently discontinue IBTROZI based on severity [see Dosage and Administration (2.4)].

5.2 Interstitial Lung Disease/Pneumonitis

IBTROZI can cause severe, life-threatening, or fatal interstitial lung disease (ILD) or pneumonitis.

In the pooled safety population [see Adverse Reactions (6.1)], interstitial lung disease (ILD)/pneumonitis occurred in 2.3% of patients treated with IBTROZI, including Grade 3 or 4 in 1.1% of patients. The median time to first onset of ILD/pneumonitis was 3.8 months (range: 12 days to 11.8 months).

ILD/pneumonitis led to dose interruption of IBTROZI in 1.1% of patients. ILD/pneumonitis required dose reduction in 0.6% of patients and permanent discontinuation of IBTROZI in 0.6% of patients. One fatal ILD case occurred in a patient who received 400 mg once daily dose of IBTROZI.

Monitor patients for new or worsening pulmonary symptoms indicative of ILD/pneumonitis. Immediately withhold IBTROZI in patients with suspected ILD/pneumonitis. Withhold, then reduce the dose or permanently discontinue IBTROZI if Grade ≥2 ILD/pneumonitis is confirmed [see Dosage and Administration (2.4)].

5.3 QTc Interval Prolongation

IBTROZI can cause QTc interval prolongation, which can increase the risk for ventricular tachyarrhythmias (e.g., torsades de pointes) or sudden death. IBTROZI prolongs the QTc interval in a concentration-dependent manner [see Clinical Pharmacology (12.2)].

In the pooled safety population [see Adverse Reactions (6.1)], of the 351 patients who underwent at least one post baseline ECG assessment, 13% experienced an increase in QTcF of >60 msec compared to baseline after receiving IBTROZI and 2.6% had an increase in QTcF to >500 msec. Overall, 3.4% of patients had Grade ≥3 QTc interval prolongation. The median time from the first dose of IBTROZI to the onset of ECG QT prolongation was 22 days (range: 1 day to 38.7 months). QTc prolongation led to dose interruption and dose reduction, each in 2.8% of patients treated with IBTROZI.

Monitor ECGs and electrolytes prior to administration of IBTROZI, and then periodically thereafter as clinically indicated during treatment. Adjust the frequency of monitoring based on risk factors such as known long QT syndromes, clinically significant bradyarrhythmias, severe or uncontrolled heart failure, and concomitant medications associated with QTc interval prolongation.

Significant prolongation of the QTc interval may occur when IBTROZI is taken with food, strong and moderate CYP3A inhibitors, and/or drugs with a known potential to prolong QTc. Administer IBTROZI on an empty stomach. Avoid coadministration of IBTROZI with strong and moderate CYP3A inhibitors and/or drugs with a known potential to prolong QTc [see Dosage and Administration (2.3), Drug Interactions (7.1, 7.2)].

Withhold, then resume at the same or reduced dose, or permanently discontinue IBTROZI based on severity [see Dosage and Administration (2.4)].

5.4 Hyperuricemia

IBTROZI can cause hyperuricemia.

In the pooled safety population [see Adverse Reactions (6.1)], 14% of patients treated with IBTROZI experienced hyperuricemia reported as an adverse reaction, with 16% of these patients requiring urate-lowering medication without pre-existing gout or hyperuricemia. Hyperuricemia Grade ≥3 occurred in one patient. The median time to first onset of hyperuricemia was 2.1 months (range: 7 days to 35.8 months). Hyperuricemia leading to dose interruption occurred in 0.3% of patients.

Monitor serum uric acid levels prior to administration of IBTROZI and periodically during treatment. Initiate treatment with urate-lowering medications as clinically indicated. Withhold, then resume at the same or reduced dose, or permanently discontinue IBTROZI based on severity [see Dosage and Administration (2.4)].

5.5 Myalgia with Creatine Phosphokinase Elevation

IBTROZI can cause myalgia with or without creatine phosphokinase (CPK) elevation.

In the pooled safety population [see Adverse Reactions (6.1)], myalgia occurred in 10% of patients treated with IBTROZI. The median time to first onset of myalgia was 11 days (range: 2 days to 10 months).

Concurrent myalgia with increased CPK within a 7-day time period was observed in 0.9% of patients. IBTROZI was interrupted in one patient (0.3%) with myalgia, who also presented with concurrent CPK elevation.

Advise patients to report any unexplained muscle pain, tenderness, or weakness. Monitor serum CPK levels during IBTROZI treatment every 2 weeks during the first month of treatment and then as clinically indicated in patients reporting unexplained muscle pain, tenderness, or weakness. Withhold, then resume at the same or reduced dose upon improvement [see Dosage and Administration (2.4)].

5.6 Skeletal Fractures

IBTROZI can increase the risk of fractures. ROS1 inhibitors as a class have been associated with skeletal fractures.

In the pooled safety population [see Adverse Reactions (6.1)], 3.4% of patients experienced fractures including 1.4% Grade 3. Some fractures occurred in the setting of an accidental fall or other predisposing factors such as osteoporosis, bone metastasis, and age-related degenerative conditions. Fractures involved the ribs (1.4%), spine (0.9%), femur (0.6%), humerus (0.3%), and acetabulum (0.3%). The median time to first onset of fracture was 10.7 months (range: 26 days to 29.1 months). Dose interruption occurred in 0.3% of patients.

Promptly evaluate patients with signs or symptoms (e.g., pain, changes in mobility, deformity) of fractures. There are no data on the effects of IBTROZI on healing of known fractures and risk of future fractures.

5.7 Embryo-Fetal Toxicity

Based on literature reports in humans with congenital mutations leading to changes in tropomyosin receptor kinase (TRK) signaling, findings from animal studies and its mechanism of action, IBTROZI can cause fetal harm when administered to a pregnant woman.

In animal reproduction studies, oral administration of taletrectinib to pregnant rats during the period of organogenesis caused structural abnormalities. Oral administration of taletrectinib to pregnant rabbits during the period of organogenesis resulted in embryo-fetal mortalities and structural abnormalities. Findings in both species occurred at doses resulting in exposures below or equal to the human exposure based on AUC at the recommended dose.

Advise pregnant women and females of reproductive potential of the potential risk to a fetus. Advise females of reproductive potential to use effective contraception during treatment with IBTROZI and for 3 weeks after the last dose. Advise male patients with female partners of reproductive potential to use effective contraception during treatment with IBTROZI and for 3 weeks after the last dose [see Use in Specific Populations (8.1, 8.3)].

6 ADVERSE REACTIONS

The following adverse reactions are discussed in greater detail in the WARNINGS AND PRECAUTIONS section:

- Hepatotoxicity [see Warnings and Precautions (5.1)]
- Interstitial Lung Disease/Pneumonitis [see Warnings and Precautions (5.2)]
- QTc Interval Prolongation [see Warnings and Precautions (5.3)]
- Hyperuricemia [see Warnings and Precautions (5.4)]
- Myalgia with Creatine Phosphokinase Elevation [see Warnings and Precautions (5.5)]
- Skeletal fractures [see Warnings and Precautions (5.6)]

6.1 Clinical Trials Experience

Because clinical trials are conducted under widely varying conditions, adverse reaction rates observed in the clinical trials of a drug cannot be directly compared to rates in the clinical trials of another drug and may not reflect the rates observed in practice.

The pooled safety population described in the WARNINGS AND PRECAUTIONS section and below reflects exposure to IBTROZI as a single agent at 600 mg orally once daily until disease progression or unacceptable toxicity in 352 patients with ROS1-positive NSCLC (N=337) and other solid tumors (N=15). Among the 352 patients who received IBTROZI, 68% were exposed for at least 6 months, and 47% were exposed for greater than 1 year. In this pooled safety population, the most common (≥20%) adverse reactions were diarrhea, nausea, vomiting, dizziness, rash, constipation, and fatigue. The most common (≥2%) Grade 3 or 4 laboratory abnormalities were increased ALT, increased AST, decreased neutrophils, increased creatine phosphokinase, decreased lymphocytes, increased magnesium, decreased hemoglobin, and increased triglycerides.

Locally Advanced or Metastatic ROS1-Positive NSCLC

The safety of IBTROZI was evaluated in the TRUST-I and TRUST-II studies [see Clinical Studies (14.1)]. Key eligibility criteria were histologically confirmed, locally advanced or metastatic, ROS1-positive NSCLC, ECOG performance status ≤1, and measurable disease per RECIST v1.1. Patients received IBTROZI as a single agent at 600 mg orally once daily until disease progression or unacceptable toxicity. Among patients who received IBTROZI, 68% were exposed for 6 months or longer and 47% were exposed for greater than one year.

The median age of patients who received IBTROZI was 56 years (range: 26 to 83); 56% female; 76% Asian, 15% White, 0.6% Black or African American, 8% unknown or other races; and 1.8% were of Hispanic or Latino ethnicity.

Serious adverse reactions occurred in 31% of patients who received IBTROZI. Serious adverse reactions in ≥2% of patients included pneumonia (7%), pleural effusion (4.7%), and hepatotoxicity (2.4%). Fatal adverse reactions occurred in 18 (5%) patients who received IBTROZI, including pneumonia (2.4%), multiple organ dysfunction syndrome (0.6%), hepatotoxicity (0.6%), cardiac arrest (0.6%), cardiac failure (0.3%), cardiopulmonary failure (0.3%), respiratory failure (0.3%), and death not otherwise specified (0.3%).

Permanent discontinuation of IBTROZI was required in 7% of patients due to adverse reactions. Adverse reactions resulting in permanent discontinuation of IBTROZI in ≥2 patients were pneumonia, ILD, and hepatotoxicity.

Dosage interruptions of IBTROZI due to an adverse reaction occurred in 41% of patients. Adverse reactions which required dosage interruption in ≥5% of patients included increased AST and increased ALT.

Dose reductions of IBTROZI due to an adverse reaction occurred in 29% of patients. Adverse reactions that required dosage reductions in ≥5% of patients included increased ALT and increased AST.

Table 3 summarizes the adverse reactions in this population.

Table 3: Adverse Reactions (≥15%) in Patients with ROS1-Positive NSCLC Who Received IBTROZI in TRUST-I and TRUST-II
Adverse Reaction^1 | IBTROZI N=337
Adverse Reaction^1 | All Grades (%) | Grade 3 or 4 (%)
Gastrointestinal Disorders
Diarrheaa | 64 | 2.1
Nausea | 47 | 1.5
Vomiting | 43 | 1.5
Constipation | 21 | 0
Nervous System Disorders
Dizzinessb | 22 | 0.3
Peripheral neuropathyc | 17 | 0.3
Dysgeusiad | 15 | 0
Skin and Subcutaneous Tissue
Rashe | 22 | 1.8
General Disorders
Fatiguef | 20 | 0.9
Cardiac
Electrocardiogram QT prolonged | 19 | 3.6
Metabolism and Nutritional
Decreased appetite | 16 | 0.3
Respiratory, thoracic and mediastinal disorders
Coughg | 16 | 0
^1 Based on NCI CTCAE version 5.0
a Includes enterocolitis
b Includes vertigo, and vertigo positional
c Includes dysesthesia, hypoesthesia, neuralgia, paresthesia, and peripheral sensory neuropathy
d Includes ageusia
e Includes dermatitis, dermatitis acneiform, drug eruption, eczema, eyelid rash, palmar-plantar erythrodysesthesia syndrome, rash maculo-papular, rash papular, skin exfoliation, and drug reaction with eosinophilia and systemic symptoms (DRESS)
f Includes asthenia
g Includes productive cough

Clinically relevant adverse reactions in <15% of patients receiving IBTROZI were pneumonia, eye disorders, myalgia, skeletal fracture, ILD/pneumonitis, dermatologic adverse reactions including drug reaction with eosinophilia and systemic symptoms (DRESS), and photosensitivity reactions.

Table 4 summarizes the laboratory abnormalities.

Table 4: Select Laboratory Abnormalities (≥20%) That Worsened from Baseline in Patients with ROS1-Positive NSCLC Who Received IBTROZI in TRUST-I and TRUST-II
Laboratory Abnormality^1 | IBTROZI^2
Laboratory Abnormality^1 | All Grades (%) | Grade 3 or 4 (%)
Hematology
Hemoglobin decreased | 48 | 3.6
Lymphocytes decreased | 38 | 4.8
Neutrophils decreased | 25 | 5
Chemistry
AST increased | 87 | 10
ALT increased | 85 | 13
Creatine phosphokinase increased | 53 | 5
Cholesterol increased | 41 | 0
Triglycerides increased | 41 | 2.5
Creatinine increased | 39 | 0.3
Uric acid increased | 38 | 0
Gamma glutamyl transferase increased | 36 | 1.8
Alkaline phosphatase increased | 30 | 0
Calcium decreased | 28 | 1.8
Albumin decreased | 25 | 0.9
Bilirubin increased | 24 | 0.6
Potassium increased | 21 | 1.2
Sodium increased | 20 | 0.9
Abbreviations: ALT = alanine aminotransferase; AST = aspartate aminotransferase
^1 Based on NCI CTCAE version 5.0
^2 The denominator used to calculate the rate varied from 149 to 336 based on the number of patients with a baseline value and at least one post-treatment value.

7 DRUG INTERACTIONS

7.1 Effects of Other Drugs on IBTROZI

Strong and Moderate CYP3A Inhibitors

Avoid concomitant use with strong or moderate CYP3A inhibitors.

Taletrectinib is a CYP3A substrate. Concomitant use of IBTROZI with a strong or moderate CYP3A inhibitor increases taletrectinib exposure [see Clinical Pharmacology (12.3)], which may increase the risk of IBTROZI adverse reactions.

Strong and Moderate CYP3A Inducers

Avoid concomitant use with strong or moderate CYP3A inducers.

Concomitant use of IBTROZI with a strong or moderate CYP3A inducer decreases taletrectinib exposure [see Clinical Pharmacology (12.3)], which may reduce the effectiveness of IBTROZI.

Gastric Acid Reducing Agents

Avoid concomitant use with proton pump inhibitors (PPI) and H2 receptor antagonists. Administer locally acting antacids at least 2 hours before or 2 hours after taking IBTROZI [see Clinical Pharmacology (12.3)].

Concomitant use of a proton pump inhibitor decreases taletrectinib exposure [see Clinical Pharmacology (12.3)], which may reduce the effectiveness of IBTROZI.

7.2. Drugs That Prolong the QTc Interval

Avoid concomitant use of IBTROZI with other drug(s) with a known potential to prolong the QTc interval, such as antiarrhythmic drugs. If concomitant use cannot be avoided, adjust the frequency of monitoring as recommended [see Warnings and Precautions (5.3), Clinical Pharmacology (12.2)]. Withhold IBTROZI if the QTc interval is >500 msec or the change from baseline is >60 msec [see Dosage and Administration (2.4)].

IBTROZI causes QTc interval prolongation [see Warnings and Precautions (5.3), Clinical Pharmacology (12.2)]. Concomitant use of IBTROZI with other drugs known to prolong the QTc interval may increase the risk of QTc interval prolongation.

8 USE IN SPECIFIC POPULATIONS

8.1 Pregnancy

Risk Summary

Based on literature reports in humans with congenital mutations leading to changes in TRK signaling, findings from animal studies, and its mechanism of action [see Clinical Pharmacology (12.1)], IBTROZI can cause fetal harm when administered to a pregnant woman. Limited data from case reports with IBTROZI used in pregnant women are insufficient to inform a drug-associated risk of adverse developmental outcomes. In animal reproduction studies, oral administration of taletrectinib to pregnant rats and rabbits during the period of organogenesis resulted in embryo-fetal mortalities and structural abnormalities at exposures that were below or equal to the human exposure based on AUC at the recommended dose (see Data). Advise pregnant women of the potential risk to a fetus.

In the U.S. general population, the estimated background risk of major birth defects and miscarriage in clinically recognized pregnancies is 2% to 4% and 15% to 20%, respectively.

Data

Human Data

Published reports of individuals with congenital mutations in TRK pathway proteins suggest that decreases in TRK-mediated signaling are correlated with obesity, developmental delays, cognitive impairment, insensitivity to pain, and anhidrosis.

Animal Data

In an embryo-fetal development study, taletrectinib was administered orally to pregnant rats during the period of organogenesis from gestation day 6 to 17 at doses of 10, 30, and 100 mg/kg/day. Taletrectinib caused fetal abnormalities including abnormal ossification of the pelvis at 100 mg/kg/day (1.3 times the human exposure based on AUC at the recommended dose).

In an embryo-fetal development study, taletrectinib was administered orally to pregnant rabbits during the period of organogenesis from gestation day 6 to 19 at doses of 15, 30, and 90 mg/kg/day. Maternal lethality and increased total pregnancy loss were observed at doses ≥15 mg/kg/day (≥0.04 times the human exposure based on AUC at the recommended dose). Fetal malformations, including undeveloped or no development of eyes, nose, and mouth, ventricular malformations, thoracic vascular malformations, and skull malformations were observed at 30 mg/kg/day (0.1 times the human exposure based on AUC at the recommended dose).

8.2 Lactation

Risk Summary

There are no data on the presence of taletrectinib or its metabolites in human milk or their effects on a breastfed child or on milk production. Because of the potential for adverse reactions in breastfed children, advise women not to breastfeed during treatment with IBTROZI and for 3 weeks after the last dose.

8.3 Females and Males of Reproductive Potential

IBTROZI can cause fetal harm when administered to a pregnant woman [see Use in Specific Populations (8.1)].

Pregnancy Testing

Verify the pregnancy status of females of reproductive potential prior to initiating IBTROZI [see Use in Specific Populations (8.1)].

Contraception

Females

Advise females of reproductive potential to use effective contraception during treatment with IBTROZI and for 3 weeks after the last dose [see Nonclinical Toxicology (13.1)].

Males

Advise male patients with female partners of reproductive potential to use effective contraception during treatment with IBTROZI and for 3 weeks after the last dose [see Nonclinical Toxicology (13.1)].

Infertility

Based on findings in animals, IBTROZI may impair fertility in males and females [see Nonclinical Toxicology 13.1]. The effects on animal fertility were reversible.

8.4 Pediatric Use

The safety and effectiveness of IBTROZI in pediatric patients has not been established.

8.5 Geriatric Use

Of the 352 patients who received IBTROZI 600 mg orally once daily, 88 (25%) patients were 65 years of age and older, and 14 (4%) patients were 75 years of age and older. There were no clinically meaningful differences in safety and efficacy between patients younger than 65 years of age and patients 65 years of age or older.

11 DESCRIPTION

IBTROZI (taletrectinib) capsules contain taletrectinib adipate, a kinase inhibitor for oral use. The molecular formula for taletrectinib adipate is C23H24FN5O•C6H10O4 and the molecular weight is 551.61 g/mol. The chemical name is 3-{4-[(2R)-2-aminopropoxy]phenyl}-N-[(1R)-1-(3-fluorophenyl)ethyl]imidazo [1,2-b]pyridazin-6-amine monoadipate. The chemical structure of taletrectinib adipate is as follows:

Figure 1: Structure of Taletrectinib Adipate

(R) Indicates chiral center

Taletrectinib adipate is a white to yellowish powder and is practically insoluble or insoluble in water, anhydrous ethanol, isopropanol, acetonitrile, and n-hexane, sparingly soluble in methanol, and slightly soluble in N-methyl pyrrolidone. The aqueous solubility is pH dependent and decreases with increasing pH. The pKa1 is 5.39 and pKa2 is 8.65.

IBTROZI (taletrectinib) capsules for oral use are supplied as immediate-release hard capsules containing
272 mg of taletrectinib adipate (equivalent to 200 mg of taletrectinib free base). Inactive ingredients are colloidal silicon dioxide, low-substituted hydroxypropyl cellulose, mannitol, pregelatinized starch, and sodium stearyl fumarate.

The white opaque capsule shell contains hypromellose and titanium dioxide. The blue printing ink (SB-6008) contains butyl alcohol, dehydrated alcohol, FD&C Blue#1 Aluminum Lake, isopropyl alcohol, propylene glycol, shellac, strong ammonia solution, and titanium dioxide.

12 CLINICAL PHARMACOLOGY

12.1 Mechanism of Action

Taletrectinib is an inhibitor of tyrosine kinase ROS1, including ROS1 resistance mutations. Taletrectinib also showed inhibitory effects on tropomyosin receptor kinases (TRKs) TRKA, TRKB, and TRKC.

Fusion proteins that include ROS1 domains can drive tumorigenic potential through hyperactivation of downstream signaling pathways leading to unconstrained cell proliferation. Taletrectinib inhibited growth of cancer cells expressing ROS1 fusion genes and mutations.

In mice subcutaneously implanted with tumors harboring ROS1 fusions, including the G2032R mutation, administration of taletrectinib resulted in tumor growth inhibition. Taletrectinib had anticancer activity in an intracranial NSCLC xenograft model harboring a ROS1 fusion.

12.2 Pharmacodynamics

Exposure-response relationship

Higher taletrectinib exposure is associated with an increased risk of Grade ≥3 increased AST/ALT.

Taletrectinib exposure-response relationships for efficacy and the time course of pharmacodynamic response have not been fully characterized.

Cardiac Electrophysiology

The largest mean increase in the QTc interval was 12.8 msec (upper confidence interval of 15.4 msec) at the mean steady-state maximum concentration (Cmax,ss) after administration of IBTROZI 600 mg once daily. The increase in the QTc internal was concentration-dependent [see Warnings and Precautions (5.3)]. At plasma concentrations achieved with administration of IBTROZI 600 mg once daily with high fat food, the predicted increase in the QTc interval is 20.5 (16.3, 24.7) msec.

12.3 Pharmacokinetics

Taletrectinib pharmacokinetics (PK) were characterized at steady state for the approved recommended dosage and the PK parameters presented below are as mean (CV%), unless otherwise specified.

Taletrectinib maximum concentration (Cmax) is 476 (36%) ng/mL and systemic exposure (AUC) is 9,649 (36%) ng•h/mL. Taletrectinib Cmax and AUC increase in a dose proportional manner over the dose range of 50 mg to 1200 mg (0.08 to 2 times the approved recommended dosage). Taletrectinib accumulation is approximately 4-fold and steady state reached within 7 days.

Absorption

Taletrectinib time to maximum plasma concentration (Tmax) is 2 to 6 hours.

Effect of Food

Both taletrectinib AUC and Cmax increased by 1.5-fold following administration with high-fat food (1000 calories, 50% fat).

Distribution

The estimated apparent (oral) volume of distribution is 9,820 L.

Taletrectinib in vitro plasma protein binding is concentration-dependent and decreases with increasing taletrectinib concentrations (from 96% at 100 ng/mL to 93% at 10,000 ng/mL). The blood-to-plasma ratio is 1.3 to 1.4 in vitro.

Elimination

Taletrectinib effective half-life is approximately 66 hours with an apparent (oral) clearance of 63 L/h (36%).

Metabolism

Taletrectinib is eliminated by CYP450 and non-CYP450 (i.e., sulfation and acetylation) metabolism. CYP3A and, to a lesser extent, CYP2C8 and CYP2C9 are the CYP450 enzymes involved in taletrectinib metabolism.

Excretion

Following a single oral dose of radiolabeled taletrectinib 200 mg, 75% of the dose was recovered in feces (15% as unchanged) and 11% in urine (2.9% as unchanged).

Specific Populations

No clinically significant differences in the pharmacokinetics of taletrectinib were observed based on age (18 to 80 years), sex, mild to moderate renal impairment (eGFR 30 to 89 mL/min), or mild hepatic impairment (total bilirubin >1 to 1.5 times ULN or AST >ULN). The effect of moderate (total bilirubin >1.5 to 3 times ULN with any AST) or severe (total bilirubin >3 x ULN with any AST) hepatic impairment, severe renal impairment (eGFR<30 mL/min), or dialysis on taletrectinib pharmacokinetics is unknown.

A 30% increase in taletrectinib exposure (AUC) was observed in Asian patients compared to White patients. No clinically significant differences in the AUC were observed between White and Black patients.

Drug Interaction Studies

Clinical Studies and Model-Informed Approaches

Strong CYP3A and P-gp Inhibitors: Taletrectinib Cmax increased by 1.8-fold and AUC by 3.3-fold following concomitant administration of itraconazole (strong CYP3A and P-gp inhibitor) 200 mg daily.

Moderate CYP3A Inhibitors: Concomitant use with moderate CYP3A inhibitors (fluconazole, erythromycin, or verapamil) is predicted to increase taletrectinib AUC up to 2.6-fold and Cmax up to 1.5-fold.

Strong CYP3A Inducers and P-gp Inducers: Taletrectinib Cmax decreased by 42% and AUC by 86% following concomitant administration of rifampin (strong CYP3A and P-gp inducer) 600 mg daily.

Moderate CYP3A Inducers: Concomitant use with a moderate CYP3A inducer (efavirenz) is predicted to reduce taletrectinib AUC by 66% and its Cmax by 40%.

Proton Pump Inhibitors (PPIs): Taletrectinib displays a pH-dependent aqueous solubility [see Description (11)]. Taletrectinib Cmax decreased by 65% and AUC by 40% following concomitant administration of omeprazole (PPI) 40 mg daily.

P-gp substrates: No clinically significant difference in the exposure of digoxin (P-gp substrate) was observed when used concomitantly with taletrectinib.

In vitro Studies

CYP450 Enzymes: Taletrectinib inhibits CYP2C8, CYP2D6, and CYP3A. Taletrectinib induces CYP1A2 and CYP3A4.

Transporter Systems: Taletrectinib is a P-gp substrate. Taletrectinib inhibits P-gp, BCRP, OATP1B1, MATE1 and MATE2-K.

13 NONCLINICAL TOXICOLOGY

13.1 Carcinogenesis, Mutagenesis, Impairment of Fertility

Carcinogenesis

Carcinogenicity studies with taletrectinib were not conducted.

Mutagenesis

Taletrectinib was not mutagenic in the in vitro bacterial reverse mutation (Ames) assay and additional mutagenicity tests. Taletrectinib was not clastogenic or aneugenic in the in vivo micronucleus study in rats in bone marrow and liver.

Impairment of Fertility

In a fertility and early embryonic development study in rats, male animals were treated with taletrectinib at doses of 4, 25, or 60 mg/kg/day orally for 70 days before mating and during 13 days of the mating period. Female rats, paired with treated males, were administered taletrectinib at doses of 4, 25, or 100 mg/kg/day orally for 14 to 21 days before mating, during the mating period and up to gestational Day 6. No effects on mating or fertility in males or females were observed at doses below or equal to the human exposure based on AUC at the recommended dose. Sperm morphological abnormalities were observed in males at exposures as low as 0.03 times the human exposure based on AUC at the recommended dose.

In repeat-dose toxicity studies up to 12 weeks in duration with oral administration of taletrectinib in rats, adverse effects in reproductive organs included epithelial vacuolation of the seminal vesicle in male rats and endometrial glandular epithelium vacuolation in the uterus with cervix in female rats at exposures 4 times the human exposure based on AUC at the recommended dose for both male and female rats. Findings in the reproductive organs were reversible.

14 CLINICAL STUDIES

14.1 Locally Advanced or Metastatic ROS1-Positive NSCLC

The efficacy of IBTROZI was evaluated in 270 patients with ROS1-positive locally advanced or metastatic NSCLC who received IBTROZI at a dose of 600 mg orally once daily, enrolled in two multicenter, single-arm, open-label clinical trials: TRUST-I (NCT04395677) or TRUST-II (NCT04919811). In both trials, patients were required to have histologically confirmed, locally advanced or metastatic, ROS1-positive NSCLC, ECOG performance status of 0 or 1, and measurable disease per Response Evaluation Criteria in Solid Tumors (RECIST) v1.1. Identification of ROS1 gene fusions in tumor specimens was determined in local laboratories using next-generation sequencing (NGS), polymerase chain reaction (PCR), fluorescence in situ (FISH), or immunohistochemistry (IHC).

The major efficacy outcome measures were confirmed overall response rate (ORR) and duration of response (DOR) according to RECIST v1.1 as assessed by a blinded independent central review (BICR). Intracranial response according to modified RECIST v1.1 was assessed by BICR. Tumor assessments with imaging were performed every 6 weeks for the first 24 weeks, every 9 weeks for the following year, and every 12 weeks thereafter. The efficacy populations included 157 patients naïve to treatment with a ROS1 TKI and 113 patients who received one prior ROS1 TKI. Patients could be chemotherapy-naïve or have received prior chemotherapy for locally advanced disease.

ROS1 TKI-Naïve

TRUST-I: Among 103 patients with ROS1 TKI-naïve NSCLC treated in TRUST-I, the median age was 56 years (range: 26 to 78); 55% were female; 100% were Asian; 73% never smoked; and 81% had ECOG performance status of 1. At baseline, 91% of patients had metastatic disease; 17% of patients had CNS metastases by BICR; 96% had adenocarcinoma; and 19% of patients had prior platinum-based chemotherapy for advanced disease.

TRUST-II: Among 54 patients with ROS1 TKI-naïve NSCLC treated in TRUST-II, the median age was 57 years (range: 27 to 82); 56% were female; 65% were Asian; 22% were White; 1.9% were Black or African American; 11% were of unknown race; 1.9% were of Hispanic or Latino ethnicity; 50% never smoked; and 61% had ECOG performance status of 1. At baseline, 91% of patients had metastatic disease, 35% of patients had CNS metastases by BICR; 98% had adenocarcinoma; and 19% of patients had prior platinum-based chemotherapy for advanced disease.

Efficacy results are summarized in Table 5.

Table 5: Efficacy Results in ROS1-Positive TKI-Naïve NSCLC Patients per BICR Assessment
Efficacy Parameters | ROS1 TKI-Naïve N=157
Efficacy Parameters | TRUST-I | TRUST-II
Efficacy Parameters | n=103 | n=54
Response Rate, % (95% CI) | 90% (83, 95) | 85% (73, 93)
Complete Response | 5% | 7%
Partial Response | 85% | 78%
Duration of Response (DOR) | n= 93 | n= 46
Median DOR (95% CI) | NR (30.4, NR) | --a
Range (months) | 1.1, 46.9+ | 1.4+, 30.4+
% with DORb ≥12 months | 72 | 63
Abbreviations: CI = Confidence interval; NR = Not reached; “+” indicating ongoing response
a Median DOR not included for TRUST-II given the shorter duration of follow-up.
b Based on observed duration of response

Among 157 ROS1 TKI-naïve patients across TRUST-I and TRUST-II, 15 had measurable CNS metastases at baseline as assessed by BICR and had not received radiation therapy to the brain within 2 months prior to study entry; responses in intracranial lesions were observed in 11 patients.

ROS1 TKI-Pretreated

TRUST-I: Among the 66 patients with ROS1 TKI-pretreated NSCLC, the median age was 51 years (range: 31 to 77); 61% were female; 100% were Asian; 74% never smoked; and 71% had ECOG performance status of 1. At baseline, 97% of patients had metastatic disease, 42% of patients had CNS metastases by BICR; 92% had adenocarcinoma; 35% of patients had prior platinum-based chemotherapy for advanced disease and 100% had prior treatment with crizotinib.

TRUST-II: Among 47 patients with ROS1 TKI-pretreated NSCLC, the median age was 55 years (range: 27 to 79); 57% were female; 47% were Asian; 34% were White; 2.1% were Black or African American, 17% were of unknown or other races; 2.1% were Hispanic or Latino; 62% never smoked; and 55% had ECOG performance status of 1. At baseline, 98% of patients had metastatic disease; 57% of patients had CNS metastases by BICR; 98% had adenocarcinoma; 40% of patients had prior platinum-based chemotherapy for advanced disease, 79% had prior treatment with crizotinib, and 21% had prior treatment with entrectinib.

Efficacy results are summarized in Table 6.

Table 6: Efficacy Results in ROS1-Positive TKI-Pretreated NSCLC Patients per BICR Assessment
Efficacy Parameters | ROS1 TKI-Pretreated N=113
Efficacy Parameters | TRUST-I | TRUST-II
Efficacy Parameters | n=66 | n=47
Response Rate, % (95% CI) | 52% (39, 64) | 62% (46, 75)
Complete Response | 0% | 11%
Partial Response | 52% | 51%
Duration of Response (DOR) | n= 34 | n= 29
Median DOR (95% CI) | 13.2 (7.7, 24.9) | --a
Range (months) | 1.4, 38.7+ | 1.7+, 30.4+
% with DORb ≥6 months | 74 | 83
% with DORb ≥12 months | 44 | 45
Abbreviations: CI = Confidence interval; “+” indicating ongoing response
a Median DOR not included for TRUST-II given the shorter duration of follow-up.
b Based on observed duration of response.

Among 113 ROS1 TKI-pretreated patients, across TRUST-I and TRUST-II, 24 had measurable CNS metastases at baseline as assessed by BICR and had not received radiation therapy to the brain within 2 months prior to study entry; responses in intracranial lesions were observed in 15 patients.

Among 32 patients who had re-biopsied samples tested by next-generation sequencing after failure of a prior ROS1 TKI, 15 had resistance mutations. Responses were observed in 8 of these 15 patients; all responding patients had tumors with solvent front mutation G2032R.

16 HOW SUPPLIED/STORAGE AND HANDLING

IBTROZI is supplied as 200 mg, Size 0 white opaque hard capsules imprinted with “TAL” and “200” in blue ink in bottles of 30 capsules (NDC 84651-200-30) in a carton containing three bottles of 30 count for a total of 90 capsules per carton (NDC 84651-200-93).

Store IBTROZI at 20°C to 25°C (68°F to 77°F); excursions are permitted to 15°C to 30°C (59°F to 86°F) [see USP Controlled Room Temperature].

17 PATIENT COUNSELING INFORMATION

Advise patients to read the FDA-approved patient labeling (Patient Information).

Hepatotoxicity

- Advise patients of the risk of hepatoxicity and of the need for laboratory tests to monitor liver function during treatment with IBTROZI and to immediately contact their healthcare providers if they experience symptoms of hepatotoxicity [see Warnings and Precautions (5.1)].

Interstitial Lung Disease (ILD)/Pneumonitis

- Inform patients of the risk of ILD/pneumonitis during treatment with IBTROZI and to contact their healthcare provider immediately if they experience new or worsening pulmonary symptoms indicative of ILD/pneumonitis [see Warnings and Precautions (5.2)].

QTc Interval Prolongation

- Inform patients of the risk of QT interval prolongation during treatment with IBTROZI and to advise patients to contact their healthcare provider immediately for any symptoms of QT interval prolongation [see Warnings and Precautions (5.3)].

Hyperuricemia

- Advise patients of the risk of hyperuricemia during treatment with IBTROZI and to contact their healthcare provider if they experience signs or symptoms associated with hyperuricemia [see Warnings and Precautions (5.4)].

Myalgia with Creatine Phosphokinase Elevation

- Advise patients of the risk of myalgia with creatine phosphokinase elevation during treatment with IBTROZI and to contact their healthcare provider if they experience unexplained muscle pain, tenderness, or weakness [see Warnings and Precautions (5.5)].

Skeletal Fractures

- Inform patients of the risk of bone fractures during treatment with IBTROZI and advise patients to contact their healthcare provider immediately if they experience signs or symptoms of fracture [see Warnings and Precautions (5.6)].

Embryo-Fetal Toxicity

- Advise pregnant women and females of reproductive potential of the potential risk to a fetus. Advise females to inform their healthcare provider of a known or suspected pregnancy [see Warnings and Precautions (5.7), Use in Specific Populations (8.1, 8.3)].
- Advise females of reproductive potential to use effective contraception during treatment with IBTROZI and for 3 weeks after the last dose [see Use in Specific Populations (8.1, 8.3)].
- Advise male patients with female partners of reproductive potential to use effective contraception during treatment with IBTROZI and for 3 weeks after the last dose [see Use in Specific Populations (8.3)].

Photosensitivity

- Inform patients that IBTROZI can cause photosensitivity. Advise patients to minimize sun exposure while taking IBTROZI and to use sun protection, including broad-spectrum sunscreen, during treatment with IBTROZI and for at least 5 days after discontinuation [see Adverse Reactions (6.1)].

Lactation

- Advise women not to breastfeed during treatment with IBTROZI and for 3 weeks after the last dose [see Use in Specific Populations (8.2)].

Drug Interactions

- Advise patients to inform their healthcare providers of all concomitant medications, including prescription medicines, over-the-counter drugs, vitamins, and herbal products [see Drug Interactions (7)].
- Advise patients to avoid grapefruit or grapefruit juice while taking IBTROZI [see Dosage and Administration (2.3)].

Administration

- Advise patients to swallow IBTROZI capsules on an empty stomach, at least 2 hours before or 2 hours after food intake [see Dosage and Administration (2.3), Clinical Pharmacology (12.3)].
- Advise patients that if a dose of IBTROZI is missed or if vomiting occurs, resume IBTROZI at its regularly scheduled time the next day [see Dosage and Administration (2.3)].

Distributed by: Nuvation Bio Inc., Burlington, MA 01803
IBTROZI™ is a trademark of Nuvation Bio Inc.
© 2025 Nuvation Bio Inc. All rights reserved.
Version: 1, 06/2025

PATIENT INFORMATION
IBTROZI™ [ib-TRO-zee]
(taletrectinib)
capsules, for oral use

What is IBTROZI?
IBTROZI is a prescription medicine used to treat adults with non-small cell lung cancer (NSCLC) that has spread within your chest or to other parts of the body and is caused by an abnormal ROS1 gene.
It is not known if IBTROZI is safe and effective in children.

Before taking IBTROZI tell your healthcare provider about all of your medical conditions, including if you:

- have liver problems.
- have lung or breathing problems other than lung cancer.
- have any heart problems, including a condition called long QT syndrome.
- have gout.
- are pregnant or plan to become pregnant. IBTROZI can harm your unborn baby. Tell your healthcare provider right away if you become pregnant or think you may be pregnant during treatment with IBTROZI.
  Females who are able to become pregnant:
  - Your healthcare provider should do a pregnancy test before you start treatment with IBTROZI.
  - You should use effective birth control (contraception) during treatment and for 3 weeks after the last dose of IBTROZI.
  - Talk to your healthcare provider about birth control methods that may be right for you.
  Males with female partners who are able to become pregnant:
  - You should use effective birth control (contraception) during treatment and for 3 weeks after the last dose of IBTROZI.
  - are breastfeeding or plan to breastfeed. It is not known if IBTROZI passes into your breast milk. Do not breastfeed during treatment and for 3 weeks after the last dose of IBTROZI. Talk to your healthcare provider about the best way to feed your baby during this time.

Tell your healthcare provider about all the medicines you take, including prescription and over-the-counter medicines, vitamins, or herbal supplements.
IBTROZI may affect the way other medicines work, and other medicines may affect how IBTROZI works.
You should not start or stop any medicine before you talk with your healthcare provider that prescribed IBTROZI.

How should I take IBTROZI?

- Take IBTROZI exactly as your healthcare provider tells you to take it. Do not change your dose or stop taking IBTROZI unless your healthcare provider tells you to.
- Take IBTROZI on an empty stomach. Do not eat food for at least 2 hours before or 2 hours after taking IBTROZI.
- Take IBTROZI at about the same time each day.
- Swallow IBTROZI capsules whole. Do not open, crush, chew or dissolve the capsule before swallowing.
- Avoid taking proton pump inhibitor (PPI), or H2 blocker medicine. If you take an antacid, take it at least 2 hours before or 2 hours after taking IBTROZI.
- If you miss a dose or vomit at any time after taking a dose of IBTROZI, take your next dose at your regularly scheduled time the next day.

What should I avoid while taking IBTROZI?

- You should limit time in the sun during treatment with IBTROZI. IBTROZI may make your skin sensitive to sunlight. Wear a hat and clothes that cover your skin and use sunscreen with sun protective factor (SPF) if you are in the sun during treatment with IBTROZI and for at least 5 days after your last dose of IBTROZI.
- You should avoid grapefruit, grapefruit juice, or products that contain grapefruit during your treatment with IBTROZI. Grapefruit may increase the amount of IBTROZI in your blood, which may increase the risk of IBTROZI side effects.

What are the possible side effects of IBTROZI?
IBTROZI can cause serious side effects, including:

- Liver problems. Changes in liver function can happen during treatment with IBTROZI and can lead to liver injury and death. Your healthcare provider will do blood tests to check your liver function before starting, every 2 weeks during the first 2 months of treatment, then monthly as needed during your treatment with IBTROZI. Tell your healthcare provider right away if you develop signs and symptoms of liver problems including:
  - yellowing of your skin or the white part of your eyes (jaundice)
  - dark or “tea-colored” urine
  - light-colored stools (bowel movements)
  - loss of appetite
  - nausea or vomiting
  - pain on the upper right side of your stomach
  - feeling tired or weak
- Lung problems. IBTROZI can cause lung problems that are severe, life-threatening or lead to death. Tell your healthcare provider right away if you have any new or worsening symptoms of lung problems, including trouble breathing, shortness of breath, cough (with or without mucus), or fever.
- Changes in the electrical activity of your heart called QT prolongation. QT prolongation can cause irregular heartbeats that can be life-threatening. Your healthcare provider will do tests before and during your treatment with IBTROZI to check the electrical activity of your heart and your body salts (electrolytes). Tell your healthcare provider right away if you feel faint, lightheaded, dizzy, or feel your heart beating irregularly or fast during your treatment with IBTROZI. These may be symptoms related to QT prolongation.
- Increased uric acid level in your blood (hyperuricemia). Your healthcare provider will check your uric acid blood level before and during your treatment with IBTROZI. Your healthcare provider may prescribe medicine to lower uric acid if needed. Tell your healthcare provider if you develop any of the following symptoms of hyperuricemia:
  - red, hot, tender or swollen joints, especially in your big toe
  - pain in your stomach-area
  - nausea or vomiting
  - pink or brown urine
- Muscle pain, tenderness, and weakness (myalgia). IBTROZI can cause myalgia with or without an increase in the level of an enzyme in your blood called creatine phosphokinase (CPK), which may be a sign of muscle damage. Your healthcare provider will do blood tests to check your CPK blood levels every 2 weeks during the first month and as needed if you experience unexplained muscle pain, tenderness, or weakness during your treatment with IBTROZI. Tell your healthcare provider if you develop unexplained muscle pain, tenderness, or weakness.
- Bone fractures. IBTROZI can increase your risk of bone fractures. Bone fractures may happen with or without a fall or other injury. Tell your healthcare provider if you develop pain, changes in movement, or bone abnormalities.

The most common side effects of IBTROZI include:

  - diarrhea
  - nausea
  - vomiting
  - dizziness
  - rash
  - constipation
  - tiredness
  - changes in your liver function tests
  - decreased white blood cell levels

IBTROZI may cause fertility problems in males and females. Talk to your healthcare provider if this is a concern for you.

Your healthcare provider may decrease your dose, temporarily stop, or completely stop your treatment with IBTROZI if you have serious side effects.
These are not all the possible side effects of IBTROZI.
Call your doctor for medical advice about side effects. You may report side effects to FDA at 1-800-FDA-1088.

How should I store IBTROZI?

- Store IBTROZI at room temperature between 68°F to 77°F (20°C to 25°C).

Keep IBTROZI and all medicines out of the reach of children.

General information about the safe and effective use of IBTROZI.
Medicines are sometimes prescribed for purposes other than those listed in a Patient Information leaflet. Do not use IBTROZI for a condition for which it was not prescribed. Do not give IBTROZI to other people, even if they have the same symptoms that you have. It may harm them. You can ask your pharmacist or healthcare provider for information about IBTROZI that is written for health professionals.

What are the ingredients of IBTROZI?
Active ingredient: taletrectinib adipate
Inactive ingredients: colloidal silicon dioxide, low-substituted hydroxypropyl cellulose, mannitol, pregelatinized starch, sodium stearyl fumarate. Capsule shell contains hypromellose and titanium dioxide. Blue printing ink contains butyl alcohol, dehydrated alcohol, FD&C Blue#1 Aluminum Lake, isopropyl alcohol, propylene glycol, shellac, strong ammonia solution, and titanium dioxide.
Distributed by: Nuvation Bio Inc., Burlington, MA 01803
IBTROZI™ is a trademark of Nuvation Bio Inc.
© 2025 Nuvation Bio Inc. All rights reserved.
For more information, go to www.IBTROZI.com or call 1-844-688-4550.

This Patient Information has been approved by the U.S. Food and Drug Administration.

Version 1

Issued: 06/2025

Principal Display Panel – 200 mg Carton Label

NDC 84651-200-93

90 Capsules

Contains three bottles
of 30 capsules per bottle.

IBTROZI™

(taletrectinib) capsules

200 mg

Swallow capsules whole

Rx Only

Nuvation Bio